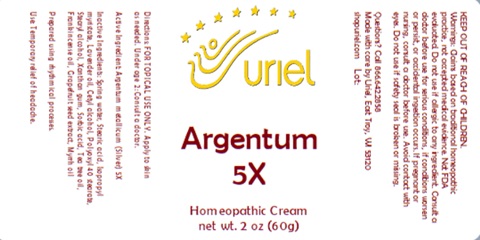 DRUG LABEL: Argentum 5
NDC: 48951-1084 | Form: CREAM
Manufacturer: Uriel Pharmacy Inc.
Category: homeopathic | Type: HUMAN OTC DRUG LABEL
Date: 20241114

ACTIVE INGREDIENTS: SILVER 5 [hp_X]/1 g
INACTIVE INGREDIENTS: FRANKINCENSE OIL; MYRRH OIL; CITRUS PARADISI SEED; TEA TREE OIL; STEARIC ACID; ISOPROPYL MYRISTATE; LAVENDER OIL; CETYL ALCOHOL; WATER; POLYOXYL 40 STEARATE; STEARYL ALCOHOL; XANTHAN GUM; SORBIC ACID

Argentum 5

INDICATIONS AND USAGE

Directions: FOR TOPICAL USE ONLY.

DOSAGE AND ADMINISTRATION

Apply to skin as needed. Under age 2: Consult a doctor.

Active Ingredient: Argentum metallicum (Silver) 5X

INACTIVE INGREDIENT

Inactive Ingredients: Spring water, Stearic acid, Isopropyl myristate, Lavender oil, Cetyl alcohol, Polyoxyl 40 stearate, Stearyl alcohol, Xanthan gum, Sorbic acid, Tea tree oil, Frankincense oil, Grapefruit seed extract, Myrrh oil

PURPOSE

Use: Temporary relief of headache.

KEEP OUT OF REACH OF CHILDREN.

Warnings: FOR EXTERNAL USE ONLY.
Claims based on traditional homeopathic practice, not accepted medical evidence. Not FDA evaluated. Do not use if allergic to any ingredient. Consult a doctor before use for serious conditions, if conditions worsen or persist, or accidental ingestion occurs. If pregnant or nursing, consult a doctor before use. Avoid contact with eyes. Do not use if safety seal is broken or missing.

QUESTIONS

Questions? Call 866.642.2858 Made with care by Uriel, East Troy, WI 53120 shopuriel.com Lot: